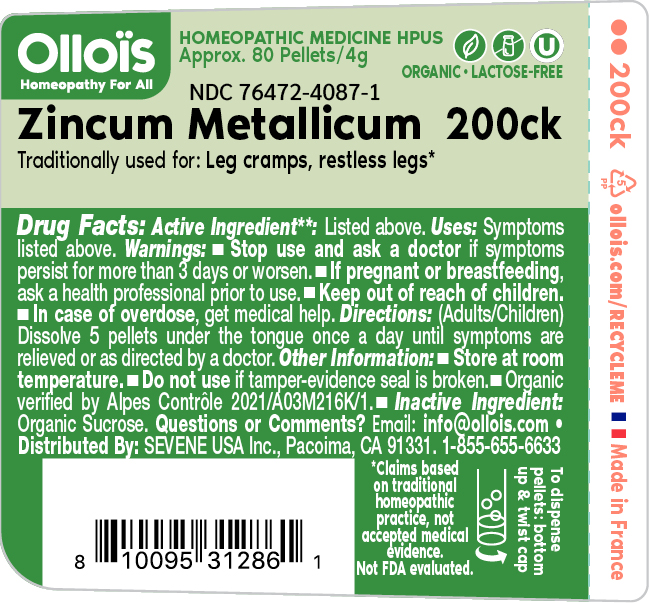 DRUG LABEL: ZINCUM METALLICUM

NDC: 76472-4087 | Form: PELLET
Manufacturer: SEVENE USA
Category: homeopathic | Type: HUMAN OTC DRUG LABEL
Date: 20250211

ACTIVE INGREDIENTS: ZINC 30 [hp_C]/1 1
INACTIVE INGREDIENTS: SUCROSE

SEVENE USA (as PLD) - ZINCUM METALLICUM 200CK (76472-4087)

ACTIVE INGREDIENT

HOMEOPATHIC DILUTION OF HPUS ZINCUM METALLICUM 200CK

TRADITIONALLY USED FOR:

LEG CRAMPS. RESTLESS LEGS*

DOSAGE AND ADMINISTRATION

Directions: (adults/children) Dissolve 5 pellets under the tongue once a day until symptoms are relieved or as directed by a physician.

USE

Condition listed above or as directed by a physician.

WARNINGS

Stop use and ask a physician if symptoms persist for more than 3 days or worsen.

PREGNANCY OR BREAST FEEDING

If pregnant or breast-feeding, ask a health professional before use.

Keep out of reach of children.

OTHER INFORMATION

Store at room temperature.

Do not use if pellet-dispenser seal is broken.

INACTIVE INGREDIENT

SUCROSE

QUESTIONS?

INFO@OLLOIS.COM * www.ollois.com * MADE IN FRANCE. NOT REVIEWED BY THE FDA AND NOT GUARANTEED TO BE EFFECTIVE. THIS HOMEOPATHIC DILUTION MAY NOT BE SUSEPTIBLE TO SCIENTIFIC MEASUREMENT.